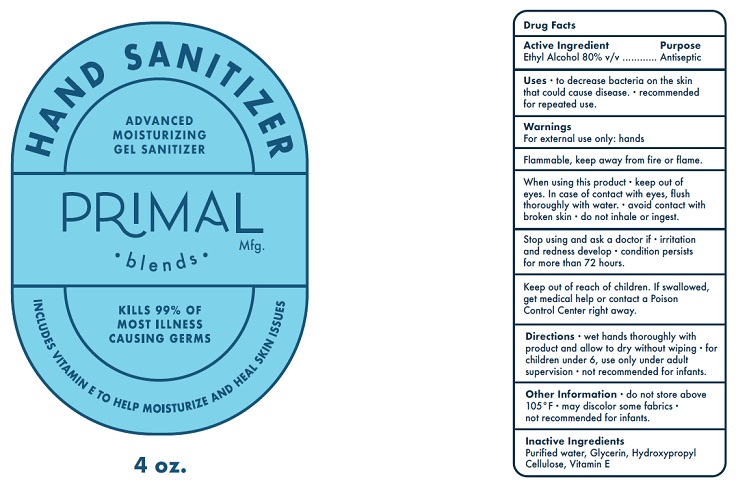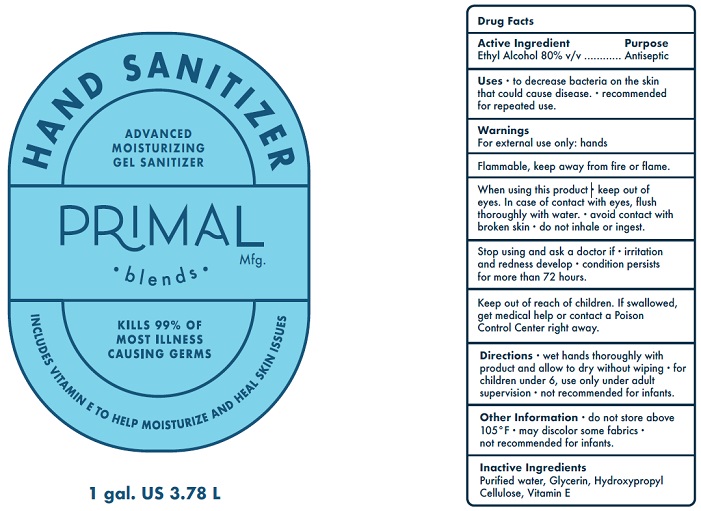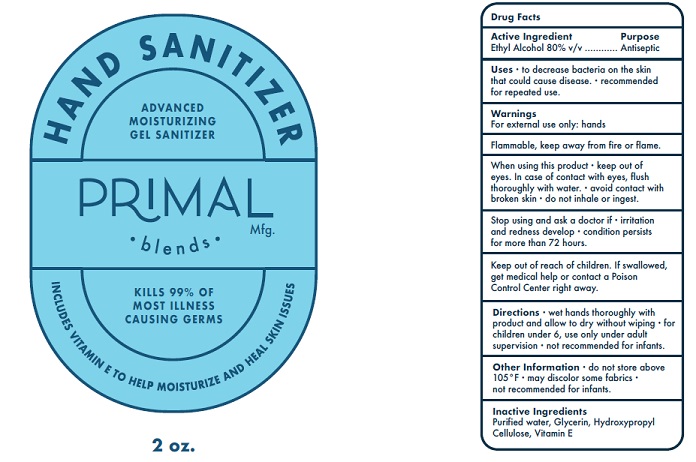 DRUG LABEL: Primal blends  advanced moisturizing gel sanitizer
NDC: 75494-006 | Form: SOLUTION
Manufacturer: Alchemy Nutra LLC
Category: otc | Type: HUMAN OTC DRUG LABEL
Date: 20200526

ACTIVE INGREDIENTS: ALCOHOL 80 mL/100 mL
INACTIVE INGREDIENTS: GLYCERIN; .ALPHA.-TOCOPHEROL; WATER; HYDROXYPROPYL CELLULOSE (110000 WAMW)

Active Ingredient

Ethyl Alcohol 80% v/v.

Purpose

Antiseptic

Uses

- to decrease bacteria on the skin that could cause disease.
- recommended for repeated use

Warnings

For external use only: hands

Flammable. Keep away from fire or flame

When using this product

- keep out of eyes. In case of contact with eyes, flush thoroughly with water.
- avoid contact with broken skin.
- do not inhale or ingest.

Stop using and ask a doctor if

- irritation and redness develop
- condition persists for more than 72 hours

Keep out of reach of children. If swallowed, get medical help or contact a Poison Control Center right away.

Directions

- wet hands thoroughly with product and allow to dry without wiping.
- for children under 6, use only under adult supervision.
- not recommended for infants.

Other Information

- do not store above 105°F.
- may discolor some fabrics.
- not recommended for infants.

Inactive ingredients

Purified water, Glycerin, Hydroxypropyl Cellulose, Vitamin E

Package Label - Principal Display Panel

59 mL

118 mL

3785 mL